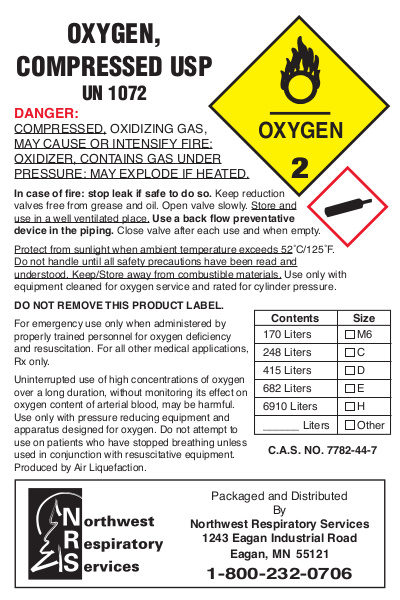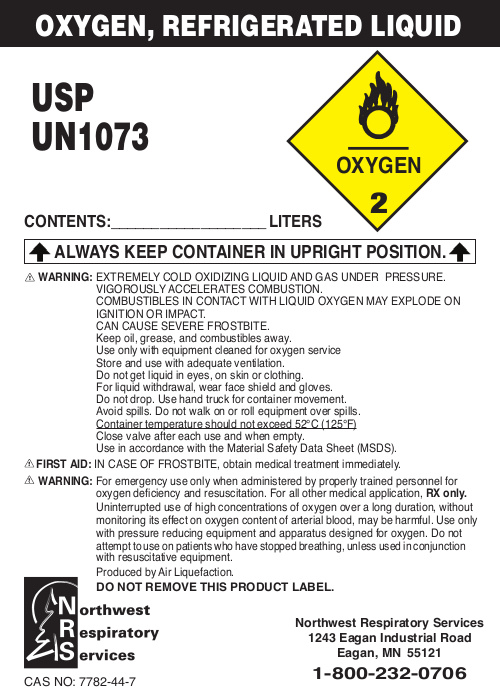 DRUG LABEL: Oxygen
NDC: 55703-001 | Form: GAS
Manufacturer: Northwest Respiratory Services
Category: prescription | Type: HUMAN PRESCRIPTION DRUG LABEL
Date: 20230417

ACTIVE INGREDIENTS: OXYGEN 992 L/1000 L

Medical oxygen drug label

Oxygen Compress USP UN 1072

Danger:

Compressed, Oxidizing Gas May Cause Or Intensify Fire:

Oxidizer, Contains Gas Under Pressure: May Explode If Heated.

In case of fire: stop leak if safe to do so. Keep reduction valves free from grease and oil. Open valve slowly. Store and use in a well ventilated place. Use a back flow preventative device in the piping. Close valve after each use and when empty.

Protect from sunlight when ambient temperature exceeds 52C/125F. Do not handle until all safety precautions have been read and understood. Keep/Store away from combustible materials. Use only with equipment cleaned for oxygen service and rated for cylinder pressure.

DO NOT REMOVE THIS PRODUCT LABEL.

for emergency use only when administered by properly trained personnel for oxygen deficiency and resuscitation. For all other medical applications Rx only.

Uninterrupted us of high concentrations of oxygen over a long duration, without monitoring its effect on oxygen content of arterial blood, may be harmful. Use only with pressure reducing equipment and apparatus designed for oxygen. Do not attempt to us on patients who have stopped breathing unless used in conjunction with resuscitative equipment. Produced by Air Liquefaction.

Please reference the image attached UN1072 label.jpg

Oxygen Refridgerated Liquid USP UN1073

CONTENTS:___________________ LITERS
OXYGEN, REFRIGERATED LIQUID
ALWAYS KEEP CONTAINER IN UPRIGHT POSITION.

WARNING: EXTREMELY COLD OXIDIZING LIQUID AND GAS UNDER PRESSURE.
VIGOROUSLY ACCELERATES COMBUSTION.
COMBUSTIBLES IN CONTACT WITH LIQUID OXYGEN MAY EXPLODE ON
IGNITION OR IMPACT.
CAN CAUSE SEVERE FROSTBITE.
Keep oil, grease, and combustibles away.
Use only with equipment cleaned for oxygen service
Store and use with adequate ventilation.
Do not get liquid in eyes, on skin or clothing.
For liquid withdrawal, wear face shield and gloves.
Do not drop. Use hand truck for container movement.
Avoid spills. Do not walk on or roll equipment over spills.
Container temperature should not exceed 52°C (125°F)
Close valve after each use and when empty.
Use in accordance with the Material Safety Data Sheet (MSDS).
FIRST AID: IN CASE OF FROSTBITE, obtain medical treatment immediately.
WARNING: For emergency use only when administered by properly trained personnel for
oxygen deficiency and resuscitation. For all other medical application, RX only.
Uninterrupted use of high concentrations of oxygen over a long duration, without
monitoring its effect on oxygen content of arterial blood, may be harmful. Use only
with pressure reducing equipment and apparatus designed for oxygen. Do not
attempt to use on patients who have stopped breathing, unless used in conjunction
with resuscitative equipment.
Produced by Air Liquefaction.
DO NOT REMOVE THIS PRODUCT LABEL.